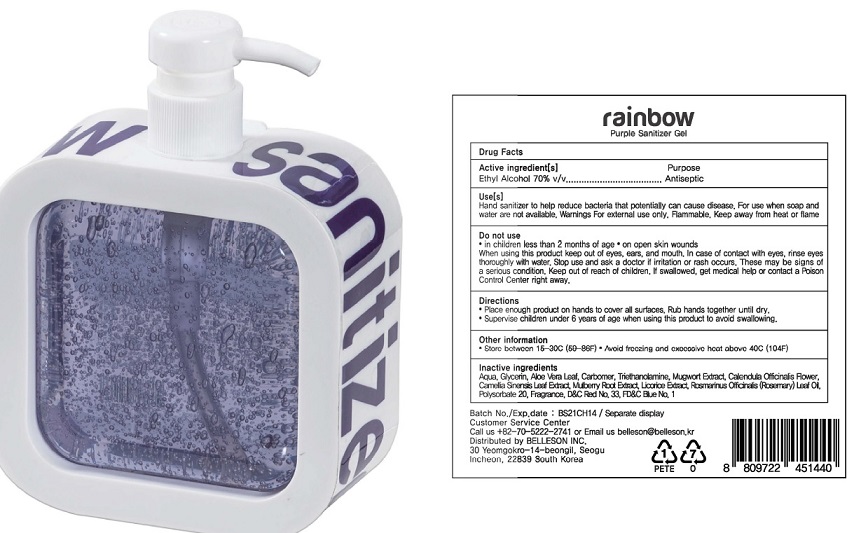 DRUG LABEL: RAINBOW HAND SANITIZER PURPLE
NDC: 75063-0014 | Form: GEL
Manufacturer: Belleson Inc
Category: otc | Type: HUMAN OTC DRUG LABEL
Date: 20211022

ACTIVE INGREDIENTS: ALCOHOL 70 mL/100 mL
INACTIVE INGREDIENTS: WATER; GLYCERIN; ALOE VERA LEAF; CALENDULA OFFICINALIS FLOWER; MORUS ALBA ROOT; POLYSORBATE 20; TROLAMINE; CARBOMER HOMOPOLYMER, UNSPECIFIED TYPE; CAMELLIA SINENSIS ROOT; LICORICE; ROSEMARY; FD&C BLUE NO. 1; D&C RED NO. 33; ARTEMISIA PRINCEPS LEAF

Active ingredient

Ethyl Alcohol 70% v/v

Purpose

Antiseptic

Uses

Hand sanitizer to help reduce bacteria that potentially can cause disease. For use when soap and
water are not available. Warnings For external use only, Flammable. Keep away from heat or flame

Warnings

Do not use
• in children less than 2 months of age

• on open skin wounds

When using this product keep out of eyes, ears, and mouth. In case of contact with eyes, rinse eyes thoroughly with water.

Stop use and ask a doctor if irritation or rash occurs. These may be signs of a serious condition.

Keep out of reach of children. If swallowed, get medical help or contact a Poison Control Center right away.

Directions

• Place enough product on hands to cover all surfaces. Rub hands together until dry.
• Supervise children under 6 years of age when using this product to avoid swallowing.

Other information

- Store between 15-30C (59-86F)

• Avoid freezing and excessive heat above 40C (104F)

Inactive ingredients

Aqua, Glycerin, Aloe vera leaf , Carbomer, Triethanolamine, Mugwort extract, Calendula officinalis flower, Camellia Sinensis Leaf Extract, Mulberry root extract, Licorice extract, Rosmarinus officinalis (Rosmary) leaf oil, Polysorbate 20, Fragrance, FD&C BLUE NO. 1, D&C RED NO. 33